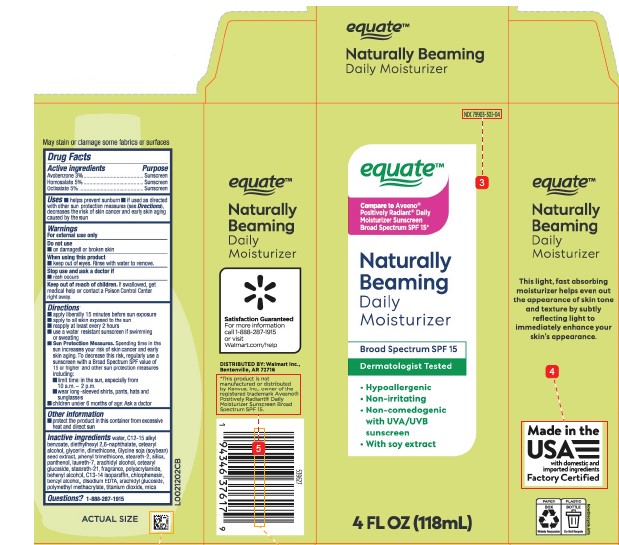 DRUG LABEL: Avbenzone, Homosalate, Octisalate
NDC: 79903-303 | Form: LOTION
Manufacturer: Walmart Inc.
Category: otc | Type: HUMAN OTC DRUG LABEL
Date: 20260227

ACTIVE INGREDIENTS: AVOBENZONE 30 mg/1 mL; HOMOSALATE 50 mg/1 mL; OCTISALATE 50 mg/1 mL
INACTIVE INGREDIENTS: WATER; ALKYL (C12-15) BENZOATE; DIETHYLHEXYL 2,6-NAPHTHALATE; CETOSTEARYL ALCOHOL; GLYCERIN; DIMETHICONE; SOYBEAN; PHENYL TRIMETHICONE; STEARETH-2; SILICON DIOXIDE; PANTHENOL; LAURETH-7; ARACHIDYL ALCOHOL; CETEARYL GLUCOSIDE; STEARETH-21; POLYACRYLAMIDE (10000 MW); DOCOSANOL; C13-14 ISOPARAFFIN; CHLORPHENESIN; BENZYL ALCOHOL; EDETATE DISODIUM; ARACHIDYL GLUCOSIDE; POLY(METHYL METHACRYLATE; 450000 MW); TITANIUM DIOXIDE; MICA

Equate D51.000/D51AA
Absolutely Beaming Daily Moisturizer

Disclaimer

May stain or damage some fabrics or surfaces

Active ingredients

Avobenzone 3%

Homosalate 5%

Octisalate 5%

Purpose

Sunscreen

Uses

- helps prevent sunburn
- if used as directed with other sun protection measures (see Directions), decreases the risk of skin cancer and early skin aging caused by the sun

Warnings

For external use only

Do not use

- on damaged or broken skin

When using this product

- keep out of the eyes. Rinse with water to remove.

Stop use and ask a doctor if

- rash occurs

Keep out of reach of children.

If swallowed, get medical help or contact a Poison Control Center right away.

Directions

- apply liberally 15 minutes before sun exposure
- apply to all skin exposed to the sun
- reapply at least every 2 hours
- use a water resistant sunscreen if swimming or sweating
- Sun Protection Measures. Spending time in the sun increases your risk of skin cancer and early skin aging. To decrease this risk, regularly use a sunscreen with a Broad Spectrum SPF value of 15 or higher and other sun protection measures including:
- limit time in the sun, especially from 10 a.m.–2 p.m.
- wear long-sleeved shirts, pants, hats and sunglasses
- children under 6 months of age: Ask a doctor

Other information

- protect the product from excessive heat and direct sun

Inactive ingredients

water, C12-15 alkyl benzoate, diethylhexyl 2,6-naphthalate, cetearyl alcohol, glycerin, dimethicone, Glycine soja (soybean) seed extract, phenyl trimethicone, steareth-2, silica, panthenol, laureth-7, arachidyl alcohol, cetearyl glucoside, steareth-21, fragrance, polyacrylamide, behenyl alcohol, C13-14 isoparaffin, chlorphenesin, benzyl alcohol, disodium EDTA, arachidyl glucoside, polymethyl methacrylate, titanium dioxide, mica

Questions?

1-888-287-1915

Side Display Panel

equate ™

NATURALLY BEAMING

DAILY MOISTURIZER

Satisfaction guaranteed

For more information call 1-888-287-1915 or visit Walmart.com/help

DISTRIBUTED BY: Walmart Inc.,

Bentonville, AR 72716

*This product is not manufactured or distributed by Kenvue, Inc., distributor of Aveeno®Positively RadiantDaily Moisturizer Sunscreen Broad Spectrum SPF 15.

Top Panel Display

equate ™

NATURALLY BEAMING

DAILY MOISTURIZER

Other Side panel display

equate ™

NATURALLY BEAMING

DAILY MOISTURIZER

This light, fast absorbing moisturizer helps even out the appearance of skin tone and texture by subtly reflecting light to immediately enhance your skin's appearance.

Made in the USA with domestic and imported ingredients

Factory Certified

PAPER BOX

Widely Recyclable

PLASTIC BOTTLE

Do Not Recycle

how2recycle.info

Principal display panel

NDC 79903-303-04

equate ™

Compare to Aveeno®Positively Radiant®Daily Moisturizer Sunscreen Broad Spectrum SPF 15*

NATURALLY BEAMING

DAILY MOISTURIZER

Broad Spectrum SPF 15

Dermatologist Tested

- Hypoallergenic
- Non-irritating
- Non-comedogenic with UVA/UVB sunscreen
- With soy extract

4 FL OZ (118 mL)